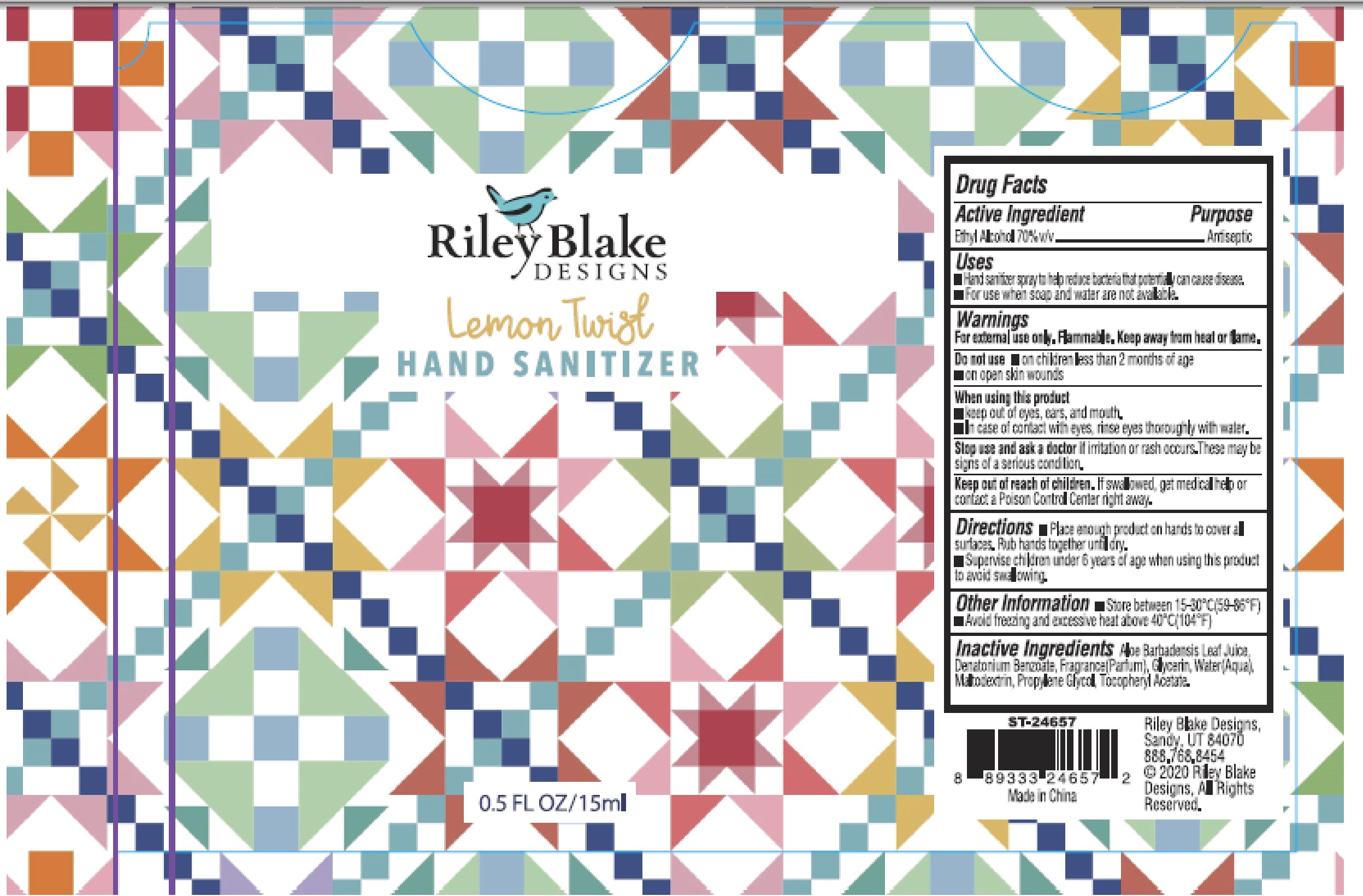 DRUG LABEL: Lemon Twist HAND SANITIZER
NDC: 80619-315 | Form: GEL
Manufacturer: Arl, Inc.
Category: otc | Type: HUMAN OTC DRUG LABEL
Date: 20210816

ACTIVE INGREDIENTS: ALCOHOL 70 mL/100 mL
INACTIVE INGREDIENTS: MALTODEXTRIN; .ALPHA.-TOCOPHEROL ACETATE; WATER; DENATONIUM BENZOATE; ALOE VERA LEAF; GLYCERIN; PROPYLENE GLYCOL

Lemon Twist
HAND SANITIZER

Active Ingredient

Ethyl Alcohol 70%vv

Purpose

Antiseptic

Uses

- Hand sanitizer spray to help reduce bacteria that potentially can cause disease.
- For use when soap and water are not available.

Warnings

For external use only. Flammable. Keep away from heat or flame.

Do not use

- on children less than 2 months of age
- on open skin wounds

When using this product

- keep out of eyes, ears, and mouth.
- In case of contact with eyes, rinse eyes thoroughly with water.

Stop use and ask a doctor if

irritation or rash occurs. These may be signs of a serious condition.

Keep out of reach of children

If swallowed, get medical help or contact a Poison Control Center right away.

Directions

- Place enough product on hands to cover all surfaces. Rub hands together until dry.
- Supervise children under 6 years of age when using this product to avoid swallowing.

Other Information

- Store between 15-30℃ (59-86F°)
- Avoid freezing and excessive heat above 40℃(104°F)

Inactive Ingredients

Aloe Barbadensis Leaf Juice, Denatonium Benzoate, Fragrance(Parfum), Glycerin, Water(Aqua), Maltodextrin, Propylene Glycol, Tocopheryl Acetate.